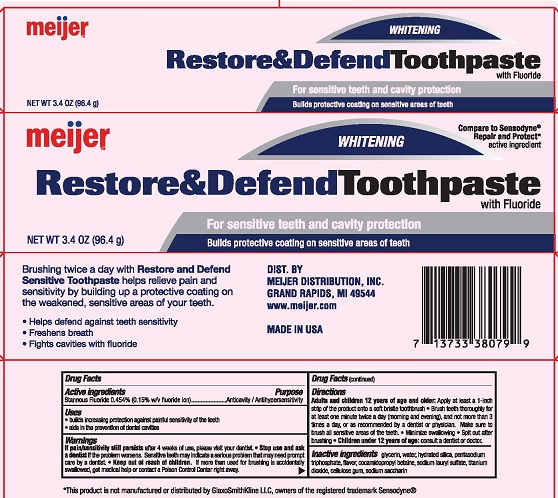 DRUG LABEL: Meijer
NDC: 41250-530 | Form: PASTE, DENTIFRICE
Manufacturer: Meijer Distribution Inc
Category: otc | Type: HUMAN OTC DRUG LABEL
Date: 20250808

ACTIVE INGREDIENTS: STANNOUS FLUORIDE 0.15 g/100 g
INACTIVE INGREDIENTS: GLYCERIN; SACCHARIN SODIUM; WATER; TITANIUM DIOXIDE; SODIUM TRIPOLYPHOSPHATE ANHYDROUS; CARBOXYMETHYLCELLULOSE SODIUM, UNSPECIFIED FORM; COCAMIDOPROPYL BETAINE; SODIUM LAURYL SULFATE; HYDRATED SILICA

5820277 Meijer Sensitive Restore & Defend Whitening

Drug Facts

Active ingredient

Stannous Fluoride 0.454% (w/v 0.15% fluoride ion)

Purpose

Anticavity/Antihypersensitivity

Uses

- builds increasing protection against painful sensitivity of the teeth to cold, heat, acids, sweets or contact
- aids in the prevention of dental cavities

Warnings

If pain/sensitivity still persists after 4 weeks of use, please visit your dentist.

Stop use and ask a dentist if:

- the problem persists or worsens. Sensitive teeth may indicate a serious problem that may need prompt care by a dentist.
- pain/sensitivity still persists after 4 weeks of use

Keep out of reach of children. If more than used for brushing is accidentally swallowed get medical help or contact a Poison Control Center right away.

Directions

Adults and children 12 years of age and older: Apply at least a 1-inch strip of the product onto a soft bristle toothbrush.

- Brush teeth thoroughly for at least one minute, preferably after each meal or at least twice a day (morning and evening) or as recommended by a dentist or physician. Make sure to brush all sensitive areas of the teeth.
- Minimize swallowing
- Spit out after brushing
- Children under 12 years of age: consult a dentist or doctor

INACTIVE INGREDIENT

Inactive ingredients glycerin, water, hydrated silica, pentasodium triphosphate, flavor, cocamidopropyl betaine, sodium lauryl sulfate, titanium dioxide, cellulose gum, sodium saccharin

DIST. BY

MEIJER DISTRIBUTION, INC.

GRAND RAPIDS, MI 49544

www.meijer.com

MADE IN USA

PACKAGE LABEL

meijer™

WHITENING

Restore & Defend Toothpaste

For sensitive teeth and cavity protection

Builds protective coating on sensitive areas of teeth

NET WT 3.4 OZ (96.4 g)